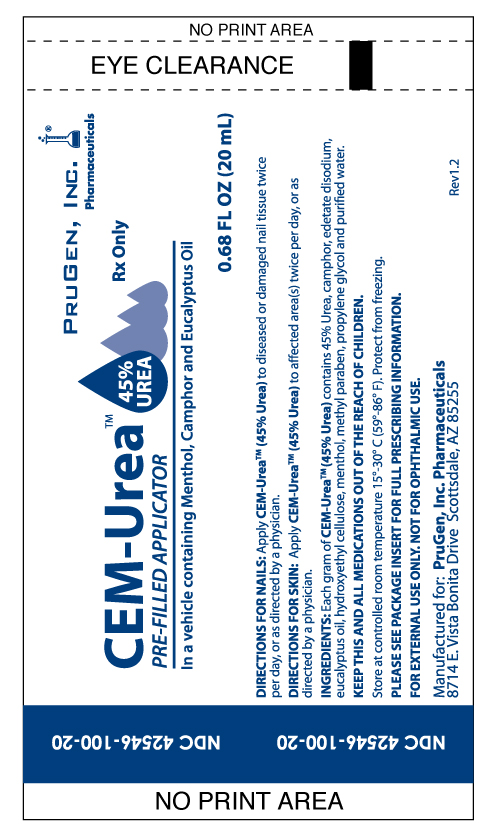 DRUG LABEL: CEM-Urea
NDC: 42546-100 | Form: SOLUTION
Manufacturer: PruGen, Inc.
Category: prescription | Type: HUMAN PRESCRIPTION DRUG LABEL
Date: 20110816

ACTIVE INGREDIENTS: UREA .45 mL/1 mL
INACTIVE INGREDIENTS: PROPYLENE GLYCOL; METHYLPARABEN; HYDROXYETHYL CELLULOSE  (3000 CPS AT 1%); WATER; EDETATE DISODIUM; EUCALYPTUS OIL; CAMPHOR (SYNTHETIC); MENTHOL

CEM-UREA TM PRE-FILLED APPLICTOR REV.1.0

DESCRIPTION

CEM-UreaTM (45% Urea) is a keratolytic emollient, which is a gentle, yet potent, tissue softener for nails and/or skin. Each gram of CEM-UreaTM (45% Urea) contains 45% Urea, camphor, edetate disodium, eucalyptus oil, hydroxyethyl cellulose, menthol, methyl paraben, propylene glycol and purified water.
Urea is a diamide of carbonic acid with the following chemical structure:

CLINICAL PHARMACOLOGY

Urea gently dissolves the intercellular matrix, which results in loosening the horny layer of skin and shedding scaly skin at regular intervals, thereby softening hyperkeratotic areas. Urea also hydrates and gently dissolves the intercellular matrix of the nail plate, which can result in the softening and eventual debridement of the nail plate.

PHARMACOKINETICS

The mechanism of action of topically applied Urea is not yet known.

INDICATIONS AND USAGE

For debridement and promotion of normal healing of hyperkeratotic surface lesions, particularly where healing is retarded by local infection, necrotic tissue, fibrinous or purulent debris or eschar. Urea is useful for the treatment of hyperkeratotic conditions such as dry, rough skin, dermatitis, psoriasis, xerosis, ichthyosis, eczema, keratosis, keratoderma, corns and calluses, as well as damaged, devitalized and ingrown nails.

CONTRAINDICATIONS

Known hypersensitivity to any of the listed ingredients.

WARNINGS AND PRECAUTIONS

For external use only. Avoid contact with eyes, lips or mucous membranes.

This medication is to be used as directed by a physician and should not be used to treat any condition other than that for which it was prescribed. If redness or irritation occurs, discontinue use.

PREGNANCY

Pregnancy Category B. Animal reproduction studies have revealed no evidence of harm to the fetus, however, there are no adequate and well-controlled studies
in pregnant women. Because animal reproductive studies are not always predictive of human response, CEM-UreaTM (45% Urea) should be given to a pregnant woman only if clearly needed.

NURSING MOTHERS

It is not known whether or not this drug is secreted in human milk. Because many drugs are secreted in human milk, caution should be exercised when CEM-UreaTM (45% Urea) is administered to a nursing woman.

KEEP THIS AND ALL MEDICATIONS OUT OF THE REACH OF CHILDREN.

ADVERSE REACTIONS

Transient stinging, burning, itching or irritation may occur and normally disappear
on discontinuing the medication.

DOSAGE AND ADMINISTRATION

DIRECTIONS FOR NAILS: Apply CEM-UreaTM (45% Urea) to diseased or damaged nail tissue twice per day, or as directed by a physician.
DIRECTIONS FOR SKIN: Apply CEM-UreaTM (45% Urea) to affected area(s) twice per day, or as directed by a physician.

HOW SUPPLIED

CEM-UreaTM (45% Urea) 20 mL tube, NDC 42546-100-20

STORAGE AND HANDLING

Store at controlled room temperature 15°-30° C (59°-86° F).
Protect from freezing.

PACKAGE LABEL

NDC 42546-100-20

CEM-Urea Pre-Filled Applicator 45% urea

In a vehicle containing Menthol, Camphor, and Eucalyptus Oil

Rx only

0.68 FL OZ (20 mL)

PruGen, Inc. Pharmaceuticals